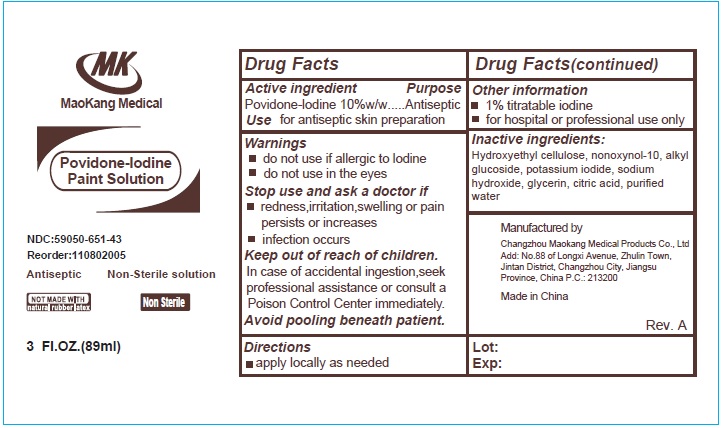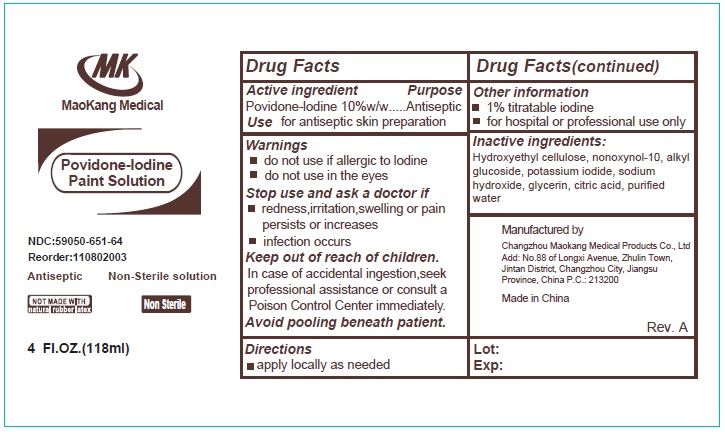 DRUG LABEL: Povidone-Iodine Paint Solution
NDC: 59050-651 | Form: SOLUTION
Manufacturer: Changzhou Maokang Medical Products Co., Ltd
Category: otc | Type: HUMAN OTC DRUG LABEL
Date: 20231110

ACTIVE INGREDIENTS: POVIDONE-IODINE 100 mg/1 mL
INACTIVE INGREDIENTS: HYDROXYETHYL CELLULOSE, UNSPECIFIED; NONOXYNOL-10; POTASSIUM IODIDE; SODIUM HYDROXIDE; GLYCERIN; CITRIC ACID MONOHYDRATE; WATER

Povidone-Iodine Paint Solution

Active ingredient

Povidone-Iodine 10%w/w

Purpose

Antiseptic

Use

for antiseptic skin preparation

Warnings

Do not use

- if allergic to Iodine
- do not use in the eyes

Stop use and ask a doctor if

- redness,irritation,swelling or pain persist or increases
- infection occurs

Keep out of reach of children.

In case of accidental ingestion, seek professional assistance or consult a Poison Control Center immediately.

Avoid pooling beneath patient.

Directions

- apply locally as needed

Other information

- 1% titratable iodine
- for hospital or professional use only

Inactive ingredients:

Hydroxyethyl cellulose, nonoxynol-10, alkyl glucoside, potassium iodide, sodium hydroxide, glycerin, citric acid, purifed water